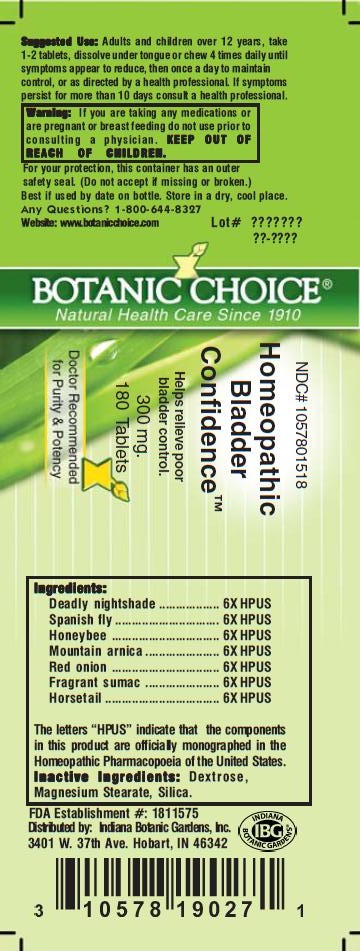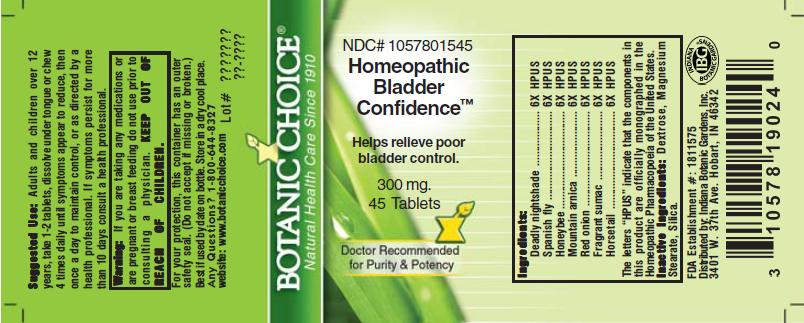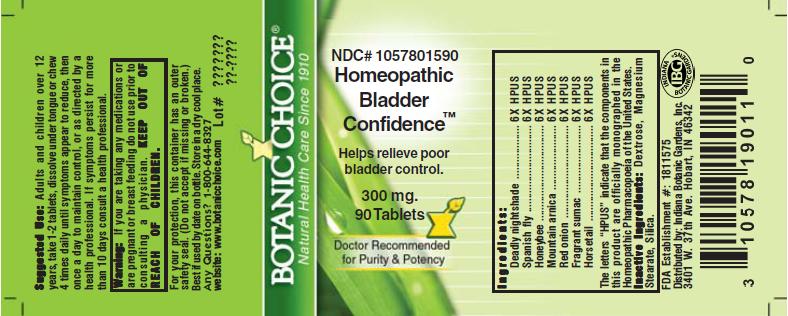 DRUG LABEL: Homeopathic Bladder Confidence Formula
NDC: 10578-015 | Form: TABLET
Manufacturer: Indiana Botanic Gardens
Category: homeopathic | Type: HUMAN OTC DRUG LABEL
Date: 20110624

ACTIVE INGREDIENTS: ATROPA BELLADONNA 6 [hp_X]/1 1; APIS MELLIFERA 6 [hp_X]/1 1; LYTTA VESICATORIA 6 [hp_X]/1 1; ARNICA MONTANA 6 [hp_X]/1 1; ONION 6 [hp_X]/1 1; RHUS AROMATICA ROOT BARK 6 [hp_X]/1 1; EQUISETUM HYEMALE 6 [hp_X]/1 1
INACTIVE INGREDIENTS: DEXTROSE; MAGNESIUM STEARATE ; SILICON DIOXIDE 

Homeopathic Bladder Confidence Formula

Ingredient s :
Deadly nightshade ............................ 6X HPUS
Spanish fly .............................. 6X HPUS
Honeybee ....................... 6X HPUS
Mountain arnica .................... 6X HPUS
Red onion ........................... 6X HPUS
Fragrant sumac ................... 6X HPUS
Horsetail ............. 6X HPUS
The letters “HPUS” indicate that the components
in this product are officially monographed in the
Homeopathic Pharmacopoeia of the United States.

PURPOSE

Helps relieve poor
bladder control.

KEEP OUT OF
REACH OF CHILDREN.

INDICATIONS AND USAGE

Helps relieve poor
bladder control.

WARNINGS

Warning: If you are taking any medications or
are pregnant or breast feeding do not use prior to
consulting a physician.

DOSAGE AND ADMINISTRATION

Suggested Use: Adults and children over 12 years, take
1-2 tablets, dissolve under tongue or chew 4 times daily until
symptoms appear to reduce, then once a day to maintain
control, or as directed by a health professional. If symptoms
persist for more than 10 days consult a health professional.

Inactive Ingredients: Dextrose,
Magnesium Stearate, Silica.

PACKAGE LABEL

NDC# 1057801518

Homeopathic
Bladder
Confidence™

Helps relieve poor
bladder control.

300 mg.
180 Tablets

For your protection, this container has an outer
safety seal. (Do not accept if missing or broken.)
Best if used by date on bottle. Store in a dry, cool place.
Any Questions? 1-800-644-8327
Website: www.botanicchoice.com

FDA Establishment #: 1811575

Distributed by: Indiana Botanic Gardens, Inc.
3401 W. 37th Ave. Hobart, IN 46342